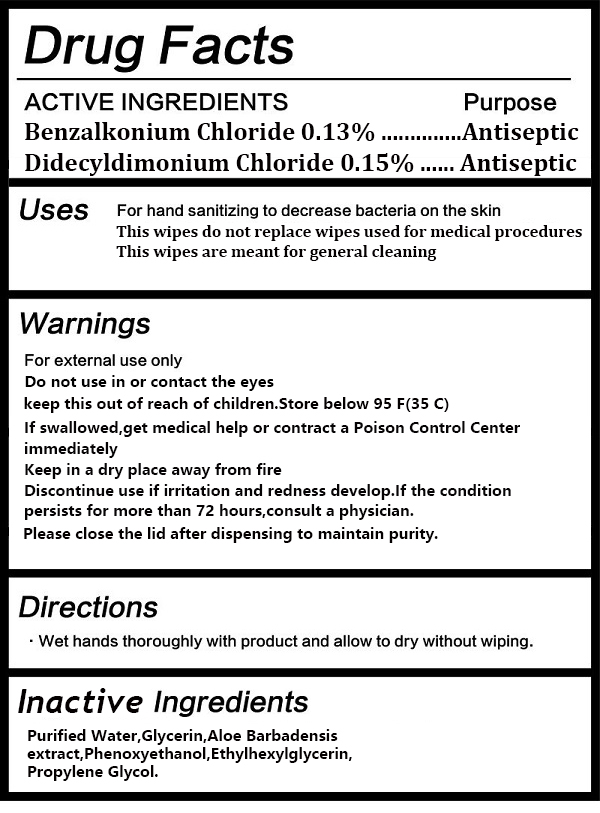 DRUG LABEL: Disinfecting  Wipes
NDC: 77850-001 | Form: CLOTH
Manufacturer: Zhejiang Aijian Sanitary Products Technology Co., Ltd.
Category: otc | Type: HUMAN OTC DRUG LABEL
Date: 20200820

ACTIVE INGREDIENTS: DIDECYLDIMONIUM CHLORIDE 0.15 g/100 g; BENZALKONIUM CHLORIDE 0.13 g/100 g
INACTIVE INGREDIENTS: PHENOXYETHANOL; ETHYLHEXYLGLYCERIN; PROPYLENE GLYCOL; GLYCERIN; WATER; ALOE VERA LEAF

77850-001 Disinfecting Wipes

ACTIVE INGREDIENT

Benzalkonium Chloride 0.13 %
Didecyldimonium Chloride 0.1 5%

PURPOSE

antiseptic

USE

For hand sanitizing to decrease bacteria on the skin
This wipes do not replace wipes used for medical procedures
This wipes are meant for general cleaning

Warning

For external use only
Do not use in or contact the eyes
keep this out of reach of children.Store below 95 F(35 C)
If swallowed,get medical help or contract a Poison Control Center
immediately
Keep in a dry place away from fire
Discontinue use if irritation and redness develop.lf the condition
persists for more than 72 hours,consult a physician.
Please close the lid after dispensing to maintain purity.

Keep this out of reach of children

Directions

. Wet hands thoroughly with product and allow to dry without wiping.

Inactive ingredients

Purified Water,Glycerin,Aloe Barbadensis
extract,Phenoxyethanol,Ethylhexylglycerin,
Propylene Glycol.